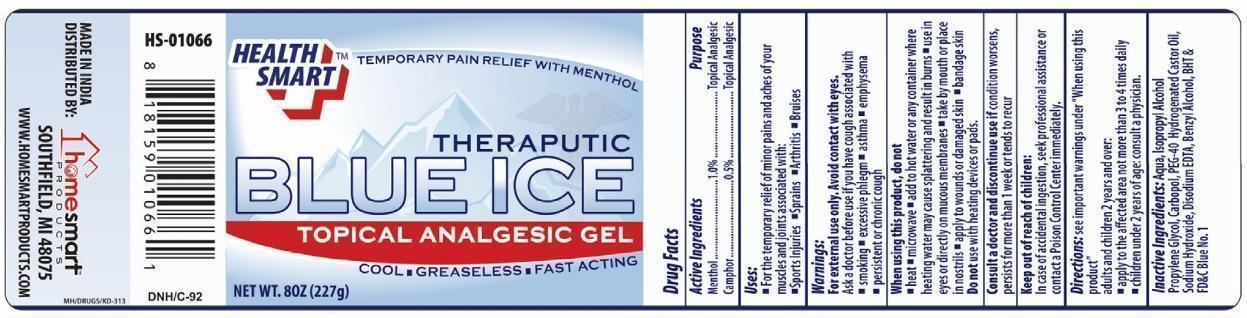 DRUG LABEL: Health Smart Blue Ice Topical Analgesic
NDC: 52862-017 | Form: GEL
Manufacturer: Home Smart Products
Category: otc | Type: HUMAN OTC DRUG LABEL
Date: 20220221

ACTIVE INGREDIENTS: MENTHOL 1 g/100 g; CAMPHOR (SYNTHETIC) 0.5 g/100 g
INACTIVE INGREDIENTS: WATER; ISOPROPYL ALCOHOL; PROPYLENE GLYCOL; CARBOMER HOMOPOLYMER TYPE B (ALLYL SUCROSE CROSSLINKED); POLYOXYL 40 HYDROGENATED CASTOR OIL; SODIUM HYDROXIDE; EDETATE DISODIUM; BENZYL ALCOHOL; BUTYLATED HYDROXYTOLUENE; FD&C BLUE NO. 1

Health Smart Blue Ice Topical Gel

Active Ingredients

Menthol 1.0%

Camphor 0.5%

Purpose

Topical Analgesic

Uses

For the temporary relief of minor pains and aches of your muscles and joints associated with:

- Sports Injuries
- Sprains
- Arthritis
- Bruises

Warnings

For external use only. Avoid contact with eyes.

Ask a doctor before use if you have cough associated with :

- smoking
- excessive phlegm
- asthma
- emphysema
- persistent or chronic cough

When using this product, do not

- heat
- microwave
- add to hot water or any container where heating water may cause splattering and result in burns
- use in eyes or directly on mucous membranes
- take by mouth or place in nostrils
- apply to wounds or damaged skin
- bandage skin

Do not use with heating devices or pads.

STOP USE

Consult a doctor and discontinue use if condition worsens, persists for more than 1 week or tends to recur.

Keep out of reach of children

In case of accidental ingestion, seek professional assistance or contact a Poison Control Center immediately.

DOSAGE AND ADMINISTRATION

Directions: see important warnings under “When using this product”

adults and children 2 years and over:

- apply to the affected area not more than 3 to 4 times daily
- children under 2 years of age: consult a physician.

Inactive Ingredients

Aqua, Isopropyl Alcohol, Propylene Glycol, Carbopol, PEG-40 Hydrogenated Castor Oil, Sodium Hydroxide , Disodium EDTA, Benzyl Alcohol, BHT & FD&C Blue No.1

PRINCIPAL DISPLAY PANEL

HEALTH SMART BLUE ICE TOPICAL ANALGESIC GEL

NET WT.8 OZ (227g)